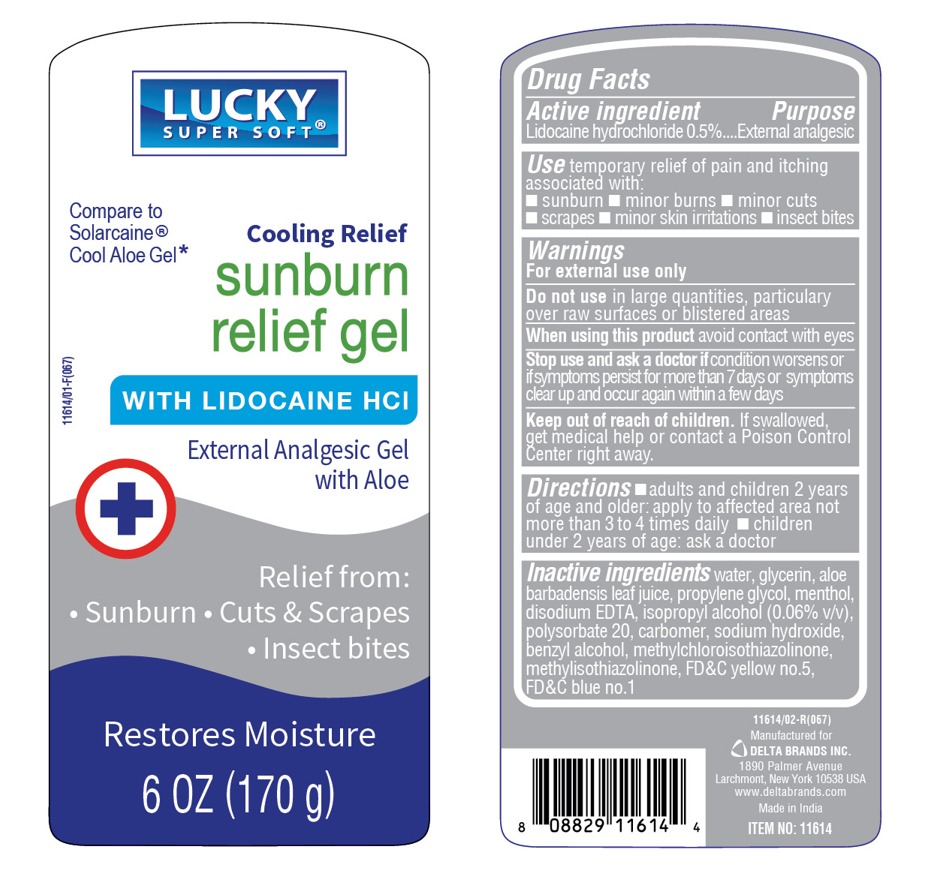 DRUG LABEL: Sunburn Relief Gel
NDC: 30400-605 | Form: GEL
Manufacturer: Jell Pharmaceuticals Pvt. Ltd
Category: otc | Type: HUMAN OTC DRUG LABEL
Date: 20250219

ACTIVE INGREDIENTS: LIDOCAINE HYDROCHLORIDE 5 mg/1 g
INACTIVE INGREDIENTS: METHYLISOTHIAZOLINONE; WATER; PROPYLENE GLYCOL; GLYCERIN; ALOE VERA LEAF; SODIUM HYDROXIDE; ISOPROPYL ALCOHOL; POLYSORBATE 20; CARBOMER HOMOPOLYMER, UNSPECIFIED TYPE; BENZYL ALCOHOL; MENTHOL; EDETATE DISODIUM; FD&C BLUE NO. 1; FD&C YELLOW NO. 5; METHYLCHLOROISOTHIAZOLINONE

Sunburn Relief Gel

Active ingredient

Lidocaine HCl 0.5%

Purpose

External analgesic

Uses

for the temporary relief of pain and itching associated with

- minor burns
- sunburn
- minor cuts
- scrapes
- insect bites
- minor skin irritations

Warnings

For external use only

When using this product

avoid contact with the eyes

Do not use

in large quantities, particularly over raw surfaces or blistered areas

Stop use and ask a doctor if

condition worsens, or if symptoms persist for more than 7 days or clean up and occur again within a few days

Keep out of reach of children

If swallowed, get medical help or contact a Poison Control Center right away.

Directions

- adults and children 2 years of age and older: apply to affected area not more than 3 to 4 times daily
- children under 2 years of age: ask a doctor

Inactive ingredients

water, propylene glycol, glycerin, Aloe Barbadensis Leaf Juice, sodium hydroxide, isopropyl alcohol, polysorbate 80, carbomer, phenoxyethanol, benzyl alcohol, menthol, disodium EDTA, blue 1, yellow 5

Principl display panel

sunburn relief gel

Pain Relieving Gel

with Aloe Vera and Lidocaine HCl